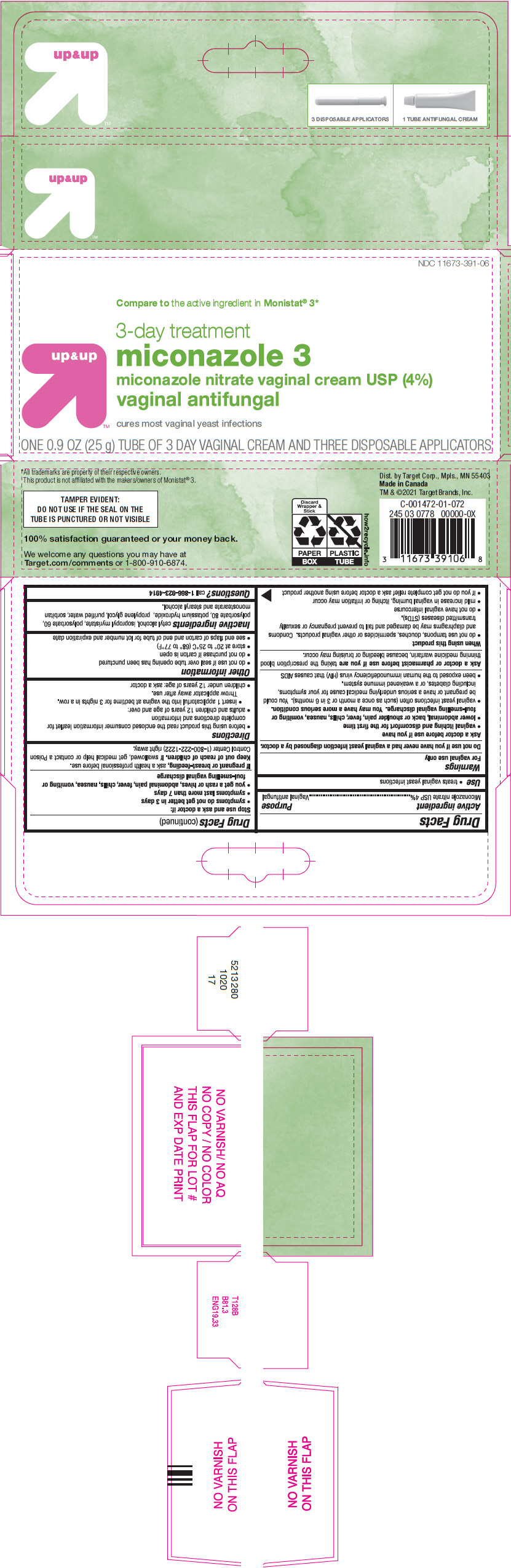 DRUG LABEL: Miconazole 3
NDC: 11673-391 | Form: CREAM
Manufacturer: TARGET Corporation
Category: otc | Type: HUMAN OTC DRUG LABEL
Date: 20250718

ACTIVE INGREDIENTS: MICONAZOLE NITRATE 40 mg/1 g
INACTIVE INGREDIENTS: CETYL ALCOHOL; ISOPROPYL MYRISTATE; POLYSORBATE 60; POLYSORBATE 80; POTASSIUM HYDROXIDE; PROPYLENE GLYCOL; WATER; SORBITAN MONOSTEARATE; STEARYL ALCOHOL

Miconazole 3

Drug Facts

Active ingredient

Miconazole nitrate USP 4%

Purpose

Vaginal antifungal

Use

- treats vaginal yeast infections

Warnings

For vaginal use only

Do not use if you have never had a vaginal yeast infection diagnosed by a doctor.

Ask a doctor before use if you have

- vaginal itching and discomfort for the first time
- lower abdominal, back or shoulder pain, fever, chills, nausea, vomiting or foul-smelling vaginal discharge. You may have a more serious condition.
- vaginal yeast infections often (such as once a month or 3 in 6 months). You could be pregnant or have a serious underlying medical cause for your symptoms, including diabetes, or a weakened immune system.
- been exposed to the human immunodeficiency virus (HIV) that causes AIDS

Ask a doctor or pharmacist before use if you aretaking the prescription blood thinning medicine warfarin, because bleeding or bruising may occur.

When using this product

- do not use tampons, douches, spermicides or other vaginal products. Condoms and diaphragms may be damaged and fail to prevent pregnancy or sexually transmitted diseases (STDs).
- do not have vaginal intercourse
- mild increase in vaginal burning, itching or irritation may occur
- if you do not get complete relief ask a doctor before using another product

Stop use and ask a doctor if:

- symptoms do not get better in 3 days
- symptoms last more than 7 days
- you get a rash or hives, abdominal pain, fever, chills, nausea, vomiting or foul-smelling vaginal discharge

PREGNANCY OR BREAST FEEDING

If pregnant or breast-feeding,ask a health professional before use.

Keep out of reach of children.If swallowed, get medical help or contact a Poison Control Center (1-800-222-1222) right away.

Directions

- before using this product read the enclosed consumer information leaflet for complete directions and information
- adults and children 12 years of age and over:
  - insert 1 applicatorful into the vagina at bedtime for 3 nights in a row.
    Throw applicator away after use.
- children under 12 years of age: ask a doctor

Other information

- do not use if seal over tube opening has been punctured
- do not purchase if carton is open
- store at 20° to 25°C (68° to 77°F)
- see end flaps of carton and end of tube for lot number and expiration date

Inactive ingredients

cetyl alcohol, isopropyl myristate, polysorbate 60, polysorbate 80, potassium hydroxide, propylene glycol, purified water, sorbitan monostearate and stearyl alcohol.

Questions?

call 1-866-923-4914

Dist. by Target Corp., Mpls., MN 55403

PRINCIPAL DISPLAY PANEL - 25 g Tube Carton

NDC 11673-391-06

Compare to the active ingredient in Monistat®3*

up&up

3-day treatment
miconazole 3
miconazole nitrate vaginal cream USP (4%)
vaginal antifungal

cures most vaginal yeast infections

ONE 0.9 OZ (25 g) TUBE OF 3 DAY VAGINAL CREAM AND THREE DISPOSABLE APPLICATORS